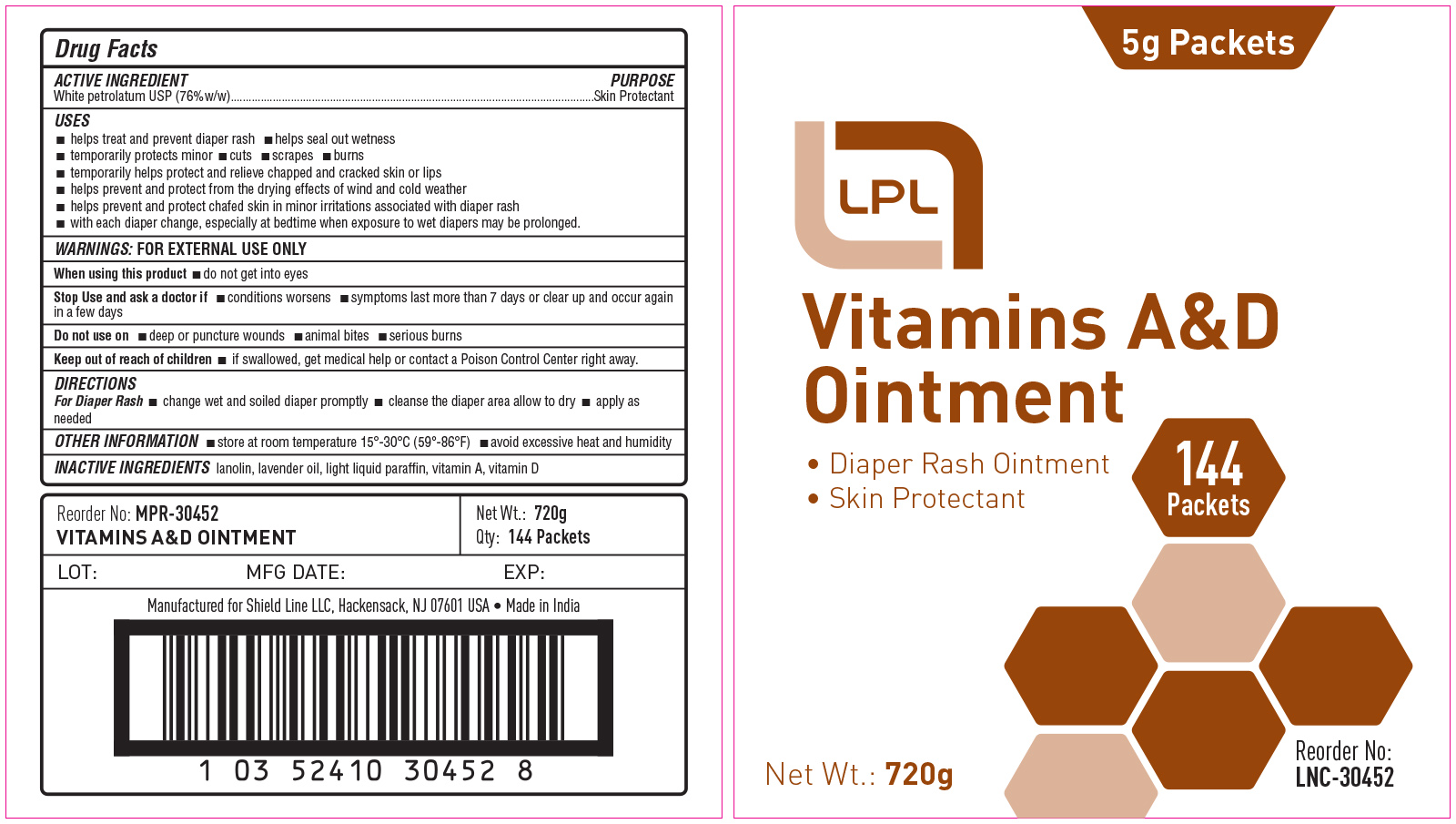 DRUG LABEL: Lincoln
NDC: 69636-3045 | Form: OINTMENT
Manufacturer: Lincoln Pharmaceuticals Ltd.
Category: otc | Type: HUMAN OTC DRUG LABEL
Date: 20170110

ACTIVE INGREDIENTS: PETROLATUM 76 g/100 g
INACTIVE INGREDIENTS: LAVENDER OIL; VITAMIN A; VITAMIN D; LANOLIN; LIGHT MINERAL OIL

ACTIVE INGREDIENT

White Petrolatum USP (76% w/w)

PURPOSE

Skin Protectant

USES

- helps treat and prevent diaper rash
- helps seal out wetness
- temporarily protects minor cuts, scrapes, burns
- temporarily helps protect and relieve chapped and cracked skin or lips
- helps prevent and protect from the drying effects of wind and cold weather
- helps prevent and protect chafed skin in minor irritations associated with diaper rash
- with each diaper change, especially at bedtime when exposure to wet diapers may be prolonged

WARNINGS:

FOR EXTERNAL USE ONLY

When using this product:

- do not get into eyes

Stop Use and ask a doctor if

- conditions worsens
- symptoms last more than 7 days or clear up and occur again in a few days

Do not use on

- deep or puncture wounds
- animal bites
- serious burns

Keep out of reach of children

- If swallowed, get medical help or contact a Poison Control Center right away

DIRECTIONS

For Diaper Rash:

change wet and soiled diaper promptly
cleanse the diaper area allow to dry
apply as needed

OTHER INFORMATION

- store at room temperature 15° - 30 °C (59-86 F)
- avoid excessive heat and humidity

INACTIVE INGREDIENTS

lanolin, lavender oil, light liquid paraffin, vitamin A, Vitamin D